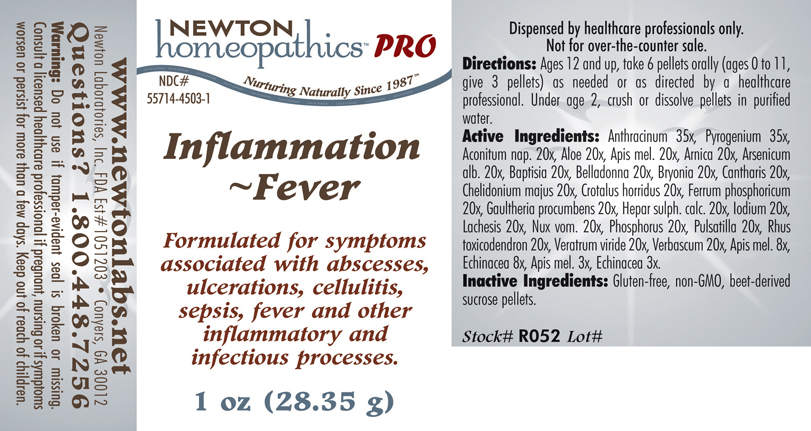 DRUG LABEL: Inflammation - Fever 
NDC: 55714-4503 | Form: PELLET
Manufacturer: Newton Laboratories, Inc.
Category: homeopathic | Type: HUMAN PRESCRIPTION DRUG LABEL
Date: 20110601

ACTIVE INGREDIENTS: Bacillus Anthracis Immunoserum Rabbit 35 [hp_X]/1 g; Rancid Beef 35 [hp_X]/1 g; Aconitum Napellus 20 [hp_X]/1 g; Aloe 20 [hp_X]/1 g; Apis Mellifera 20 [hp_X]/1 g; Arnica Montana 20 [hp_X]/1 g; Arsenic Trioxide 20 [hp_X]/1 g; Baptisia Tinctoria Root 20 [hp_X]/1 g; Atropa Belladonna 20 [hp_X]/1 g; Bryonia Alba Root 20 [hp_X]/1 g; Lytta Vesicatoria 20 [hp_X]/1 g; Chelidonium Majus 20 [hp_X]/1 g; Crotalus Horridus Horridus Venom 20 [hp_X]/1 g; Ferrosoferric Phosphate 20 [hp_X]/1 g; Gaultheria Procumbens Top 20 [hp_X]/1 g; Calcium Sulfide 20 [hp_X]/1 g; Iodine 20 [hp_X]/1 g; Lachesis Muta Venom 20 [hp_X]/1 g; Strychnos Nux-vomica Seed 20 [hp_X]/1 g; Phosphorus 20 [hp_X]/1 g; Pulsatilla Vulgaris 20 [hp_X]/1 g; Toxicodendron Pubescens Leaf 20 [hp_X]/1 g; Veratrum Viride Root 20 [hp_X]/1 g; Verbascum Thapsus 20 [hp_X]/1 g; Echinacea, Unspecified 8 [hp_X]/1 g
INACTIVE INGREDIENTS: Sucrose

Inflammation - Fever

INDICATIONS & USAGE SECTION

Inflammation - Fever Formulated for symptoms associated with abscesses, ulcerations, cellulitis, sepsis, fever and other inflammatory and infectious processes.

DOSAGE & ADMINISTRATION SECTION

Directions: Ages 12 and up, take 6 pellets orally (ages 0 to 11, give 3 pellets) as needed or as directed by a healthcare professional. Under age 2, crush or dissolve pellets in purified water.

ACTIVE INGREDIENT SECTION

Anthracinum 35x, Pyrogenium 35x, Aconitum nap. 20x, Aloe 20x, Apis mel. 20x, Arnica 20x, Arsenicum alb. 20x, Baptisia 20x, Belladonna 20x, Bryonia 20x, Cantharis 20x, Chelidonium majus 20x, Crotalus horridus 20x, Ferrum phosphoricum 20x, Gaultheria procumbens 20x, Hepar sulph. calc. 20x, Iodium 20x, Lachesis 20x, Nux vom. 20x, Phosphorus 20x, Pulsatilla 20x, Rhus toxicodendron 20x, Veratrum viride 20x, Verbascum 20x, Apis mel. 8x, Echinacea 8x, Apis mel. 3x, Echinacea 3x.

PURPOSE SECTION

Formulated for symptoms associated with abscesses, ulcerations, cellulitis, sepsis, fever and other inflammatory and infectious processes.

INACTIVE INGREDIENT SECTION

Inactive Ingredients: Gluten-free, non-GMO, beet-derived sucrose pellets.

QUESTIONS? SECTION

www.newtonlabs.net Newton Laboratories, Inc. FDA Est # 1051203 - Conyers, GA 30012
Questions? 1.800.448.7256

WARNINGS SECTION

Warning: Do not use if tamper - evident seal is broken or missing. Consult a licensed healthcare professional if pregnant, nursing or if symptoms worsen or persist for more than a few days. Keep out of reach of children.

PREGNANCY OR BREAST FEEDING SECTION

Consult a licensed healthcare professional if pregnant or nursing or if symptoms worsen or persist for more than a few days.

KEEP OUT OF REACH OF CHILDREN SECTION

Keep out of reach of children.